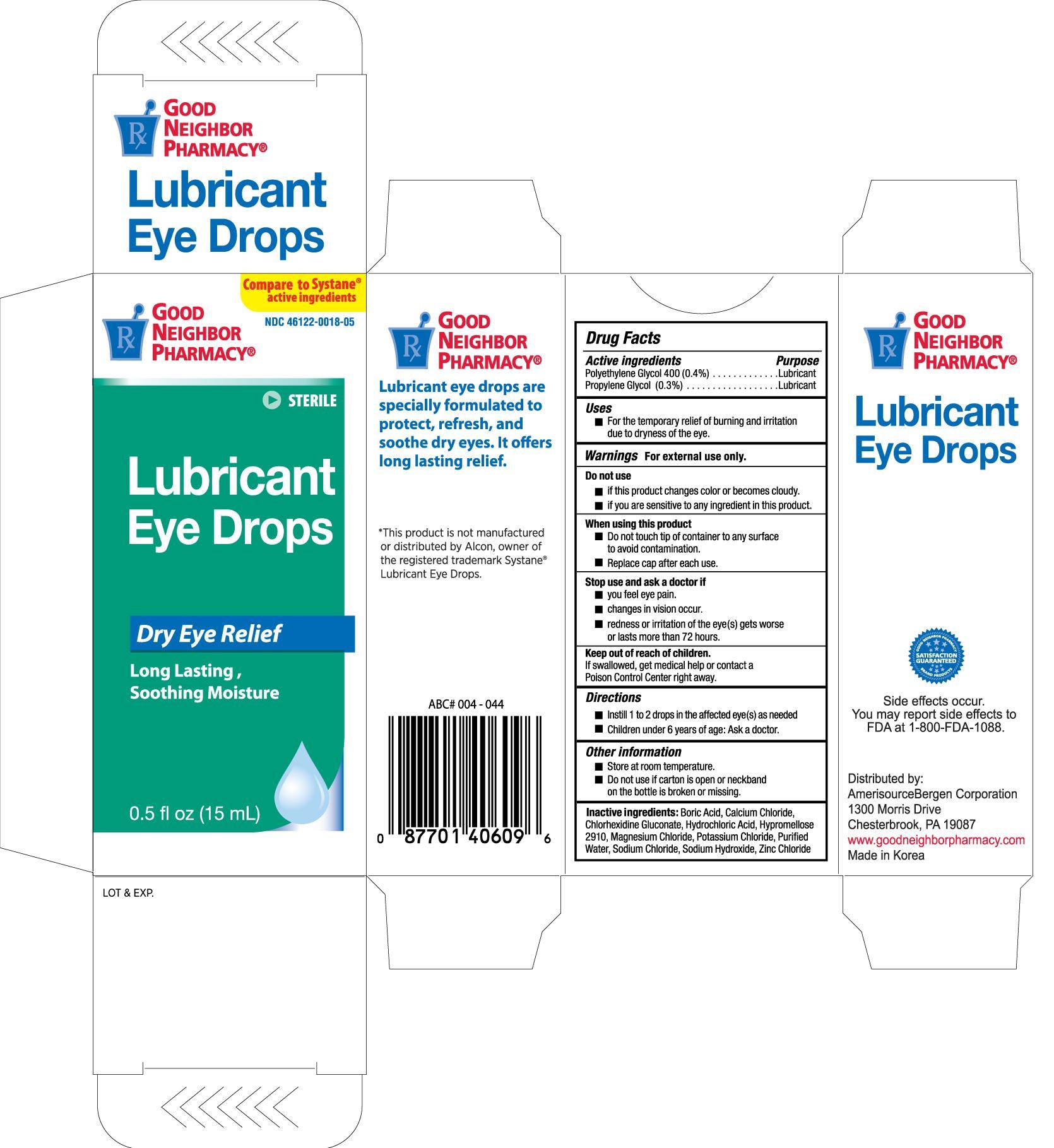 DRUG LABEL: GNP Lubricant Eye
                
NDC: 46122-018 | Form: SOLUTION/ DROPS
Manufacturer: Amerisource Bergen
Category: otc | Type: HUMAN OTC DRUG LABEL
Date: 20130630

ACTIVE INGREDIENTS: POLYETHYLENE GLYCOL 400 0.4 mg/1 mg; PROPYLENE GLYCOL 0.3 mg/1 mg
INACTIVE INGREDIENTS: BORIC ACID; CALCIUM CHLORIDE; CHLORHEXIDINE GLUCONATE; HYDROCHLORIC ACID; MAGNESIUM CHLORIDE; POTASSIUM CHLORIDE; WATER; SODIUM CHLORIDE; SODIUM HYDROXIDE; ZINC CHLORIDE

Drug Facts

Active ingredients Purpose

Polyethylene Glycol 400 (0.4%).........................................Lubricant

Propylene Glycol (0.3%)....................................................Lubricant

Uses

- For the temporary relief of burning and irritation due to dryness of the eye.

Warnings For external use only.

Do not use

- if this product changes color or becomes cloudy.
- if you are sensitive to any ingredient in this product.

When using this product

- Do not touch tip of container to any surface to avoid contamination.
- Replace cap after each use.

Stop use and ask a doctor if

- you feel eye pain.
- changes in vision occur.
- redness or irritation of the eye(s) get worse or lasts more than 72 hours.

Keep out of reach of children. If swallowed, get medical help or contact a Poison Control Center right away.

Directions

- Instill 1 to 2 drops in the affected eye(s) as needed
- Children under 6 years of age: Ask a doctor.

Other information

- Store at room temperature.
- Do not use if carton is open or neckband on the bottle is broken or missing.

INACTIVE INGREDIENT

Inactive ingredients: Boric Avid, Calcium Chloride, Chlorhexidine Gluconate, Hydrochloric Acid, Hypromellose 2910, Magnesium Chloride, Potassium Chloride, Purified Water, Sodim Chloride, Sodium Hydroxide, Zinc Chloride

DOSAGE AND ADMINISTRATION

Distributed By:

Amerisource Bergen Corporation

1300 Morris Drive

Chesterbrook, PA 19087

Made in Korea